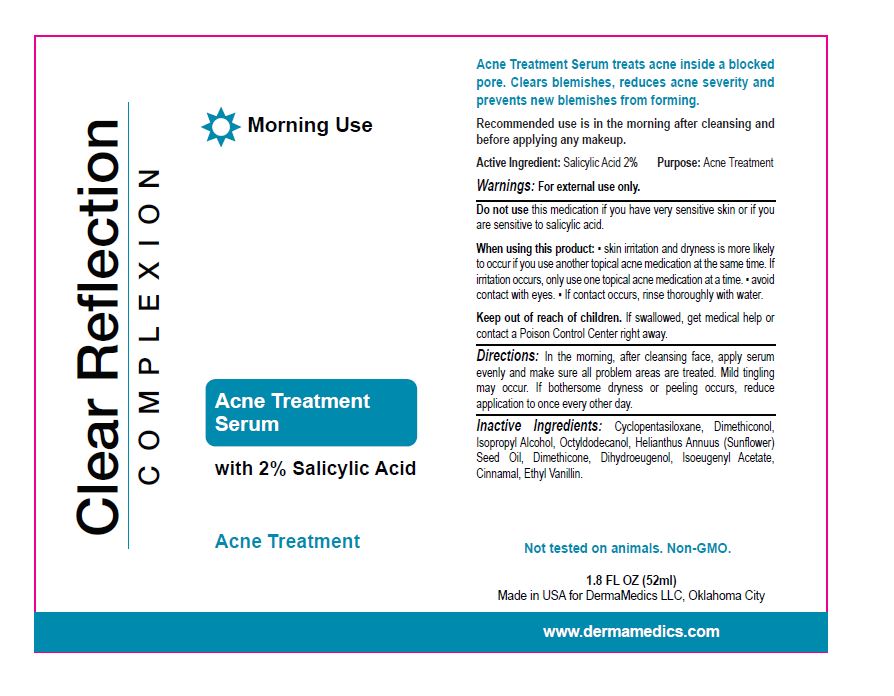 DRUG LABEL: Clear Reflection Complexion Acne Treatment Serum
NDC: 76348-685 | Form: GEL
Manufacturer: Renu Laboratories, Inc.
Category: otc | Type: HUMAN OTC DRUG LABEL
Date: 20231030

ACTIVE INGREDIENTS: SALICYLIC ACID 1.04 g/52 mL
INACTIVE INGREDIENTS: CINNAMALDEHYDE; ISOPROPYL ALCOHOL; SUNFLOWER OIL; ISOEUGENYL ACETATE; ETHYL VANILLIN; DIHYDROEUGENOL; CYCLOMETHICONE 5; OCTYLDODECANOL; DIMETHICONOL (50000 CST); DIMETHICONE 12500

Clear Reflection Complexion Acne Treatment Serum

ACTIVE INGREDIENT

2 percent Salicylic Acid

WARNINGS

For external use only.

Do not use this medication if you have very sensitive skin or if you are sensitive to salicylic acid.

WHEN USING

Skin irritation and dryness is more likely to occur if you use another topical acne medication at the same time. If irritation occurs, only use one medication at a time.

Avoid contact with the eyes

If contact occurs, rinse thoroughly with water

Keep out of reach of children. If swallowed, get medical help or contact a Poison Control Center right away.

Directions

In the morning, after cleansing face, apply serum evenly and make sure all problem areas are treated. Mild tingling may occur. If bothersome dryness occurs, reduce application to once every other day.

INACTIVE INGREDIENT

Cyclopentasiloxane, Dimethiconol, Isopropyl Alcohol, Octyldodecanol, Helianthus Annuus (Sunflower) Seed Oil, Dimethicone, Dihydroeugenol, Isoeugenyl, Cinnamal, Ethyl Vanilla.

PURPOSE

Acne Treatment

INDICATIONS AND USAGE

Recommended use is in the morning after cleansing and before applying any makeup.

QUESTIONS

Call Customer Service at 1 800 990 6552 or contact customerservice@dermamedics.com